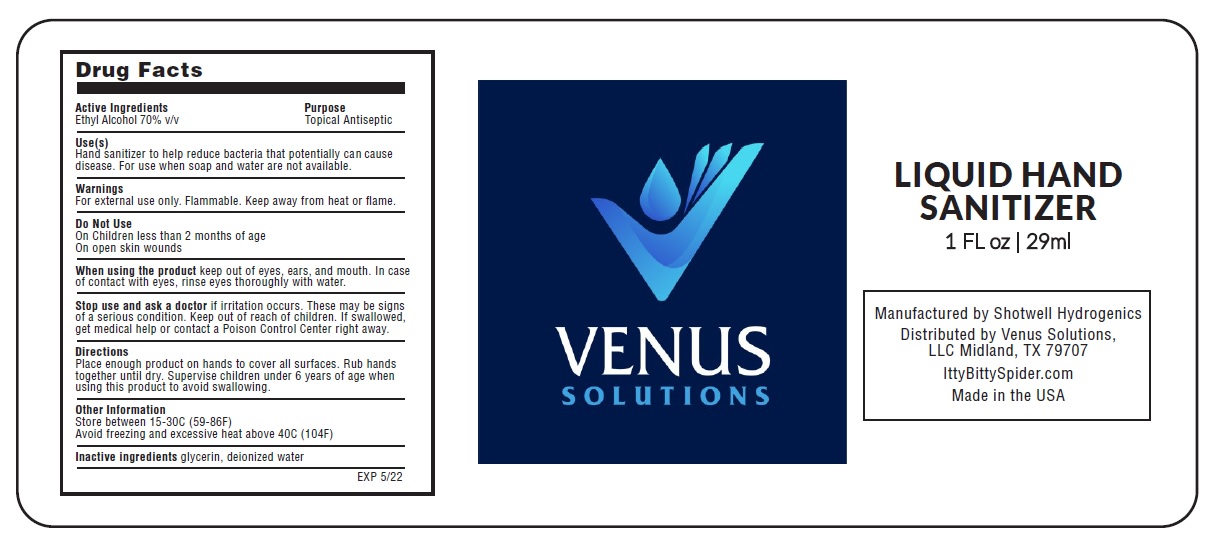 DRUG LABEL: VENUS SOLUTIONS HAND SANITIZER
NDC: 77963-001 | Form: LIQUID
Manufacturer: Venus Oilfield Solutions Llc
Category: otc | Type: HUMAN OTC DRUG LABEL
Date: 20200522

ACTIVE INGREDIENTS: ALCOHOL 70 mL/100 mL
INACTIVE INGREDIENTS: GLYCERIN; WATER

LIQUID HAND SANITIZER

Active Ingredients

Ethyl Alcohol 70% v/v

Purpose

Topical Antiseptic

Use(s)

Hand sanitizer to help reduce bacteria that potentially can cause disease. For use when soap and water are not available.

Warnings

For external use only. Flammable. Keep away from heat or ﬂame.

Do Not Use

On Children less than 2 months of age

On open skin wounds

When using the product keep out of eyes, ears, and mouth. In case of contact with eyes, rinse eyes thoroughly with water.

Stop use and ask a doctor if irritation occurs. These may be signs of a serious condition.

Keep out of reach of children. If swallowed, get medical help or contact a Poison Control Center right away.

Directions

Place enough product on hands to cover all surfaces. Rub hands together until dry. Supervise children under 6 years of age when using this product to avoid swallowing.

Other Information

Store between 15-30C (59-86F)

Avoid freezing and excessive heat above 40C (104F)

Inactive ingredients glycerin, deionized water

Manufactured by Shotwell Hydrogenics

Distributed by Venus Solutions,

LLC Midland, TX 79707

IttyBittySpider.com

Made in the USA

EXP 5/22